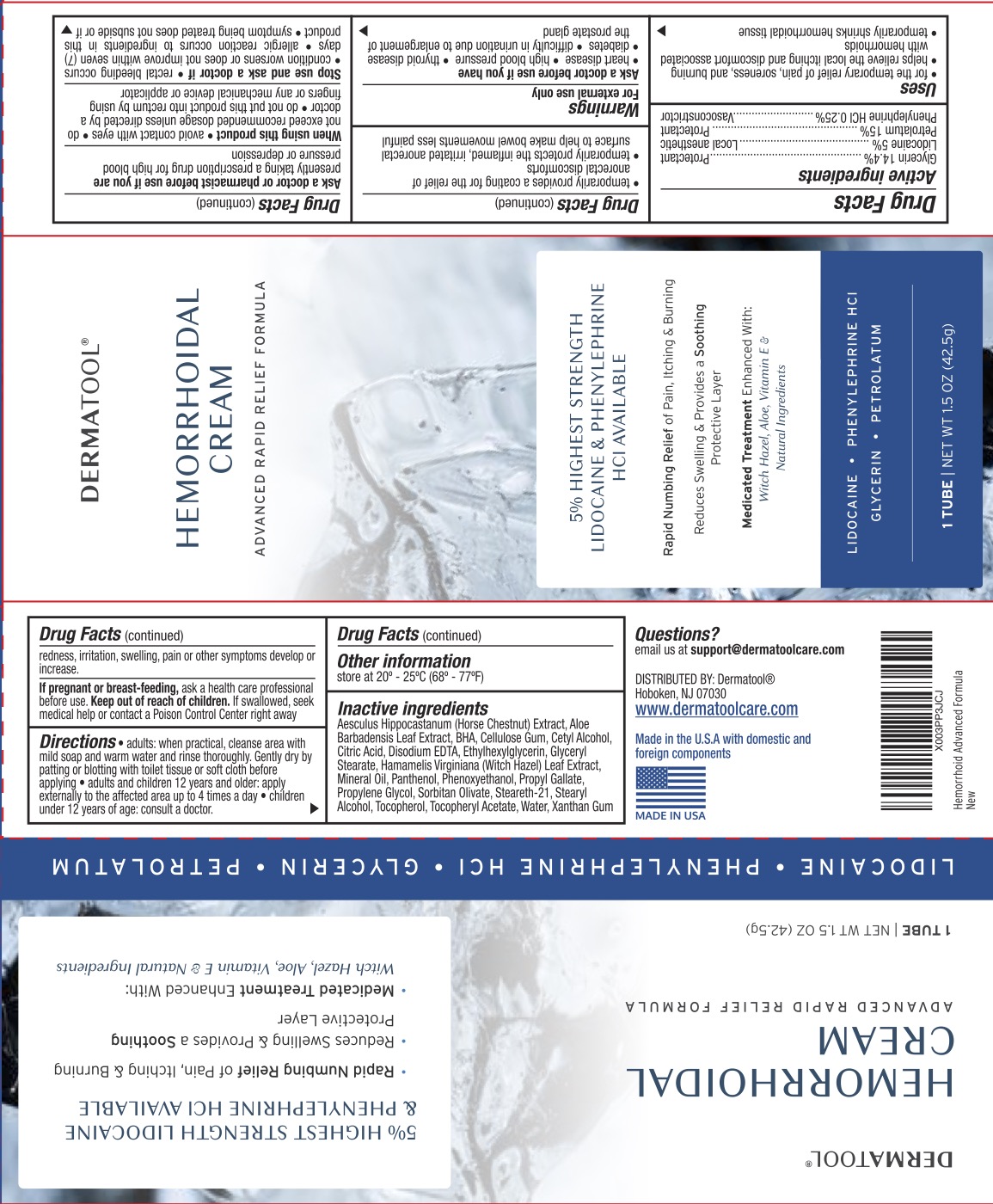 DRUG LABEL: Dermatool Hemorrhoidal
NDC: 84728-413 | Form: CREAM
Manufacturer: Papalo Group LLC
Category: otc | Type: HUMAN OTC DRUG LABEL
Date: 20260226

ACTIVE INGREDIENTS: LIDOCAINE 5 g/100 g; PETROLATUM 15 g/100 g; GLYCERIN 14.4 g/100 g; PHENYLEPHRINE HYDROCHLORIDE 0.25 g/100 g
INACTIVE INGREDIENTS: HORSE CHESTNUT; HAMAMELIS VIRGINIANA LEAF; XANTHAN GUM; MINERAL OIL; PHENOXYETHANOL; .ALPHA.-TOCOPHEROL ACETATE; CETYL ALCOHOL; CITRIC ACID MONOHYDRATE; EDETATE DISODIUM; BUTYLATED HYDROXYANISOLE; ALOE VERA LEAF; SORBITAN OLIVATE; STEARETH-21; WATER; ETHYLHEXYLGLYCERIN; GLYCERYL MONOSTEARATE; PANTHENOL; PROPYL GALLATE; PROPYLENE GLYCOL; CARBOXYMETHYLCELLULOSE SODIUM; STEARYL ALCOHOL; TOCOPHEROL

Dermatool Hemorrhoidal Cream

ACTIVE INGREDIENT

Glycerin 14.4%, Lidocaine 5%, Petrolatum 15%, Phenylephrine HCl 0.25%

PURPOSE

Anorectal/Hemorrhoidal

INDICATIONS AND USAGE

For the temporary relief of pain, soreness, and burning. Helps relieve the local itching and discomfort associated with hemorrhoids. Temporarily shrinks hemorrhoidal tissue. Temporarily provides a coating for the relief of anorectal discomforts. Temporarily protects the inflamed, irritated anorectal surface to help make bowel movements less painful.

WARNINGS

For external use only.

Ask a doctor before use if you have: heart disease, high blood pressure, thyroid disease, diabetes, or difficulty in urination due to enlargement of the prostate gland.

Ask a doctor or pharmacist before use if you are presently taking a prescription drug for high blood pressure or depression.

When using this product: avoid contact with eyes, do not exceed recommended dosage unless directed by a doctor, do not put this product into rectum by using fingers or any mechanical device or applicator.

Stop use and ask a doctor if: rectal bleeding occurs, condition worsens or does not improve within seven (7) days, allergic reaction occurs to ingredients in this product, symptom being treated does not subside or if redness, irritation, swelling, pain or other symptoms develop or increase, symptoms clear up and return within a few days.

PREGNANCY OR BREAST FEEDING

Ask a health care professional before use.

KEEP OUT OF REACH OF CHILDREN

If swallowed, seek medical help or contact a Poison Control Center right away.

DOSAGE AND ADMINISTRATION

Adults: when practical, cleanse area with mild soap and warm water and rinse thoroughly. Gently dry by patting or blotting with toilet tissue or soft cloth before applying. Adults and children 12 years and older: apply externally to the affected area up to 4 times a day. Children under 12 years of age: consult a doctor.

INACTIVE INGREDIENT

Aesculus hippocastanum (horse chestnut) extract, aloe barbadensis leaf extract, BHA, cellulose gum, cetyl alcohol, citric acid, disodium EDTA, ethylhexylglycerin, glyceryl stearate, hamamelis virginiana (witch hazel) leaf extract, mineral oil, panthenol, phenoxyethanol, propyl gallate, propylene glycol, sorbitan olivate, steareth-21, stearyl alcohol, tocopherol, tocopheryl acetate, water, xanthan gum.